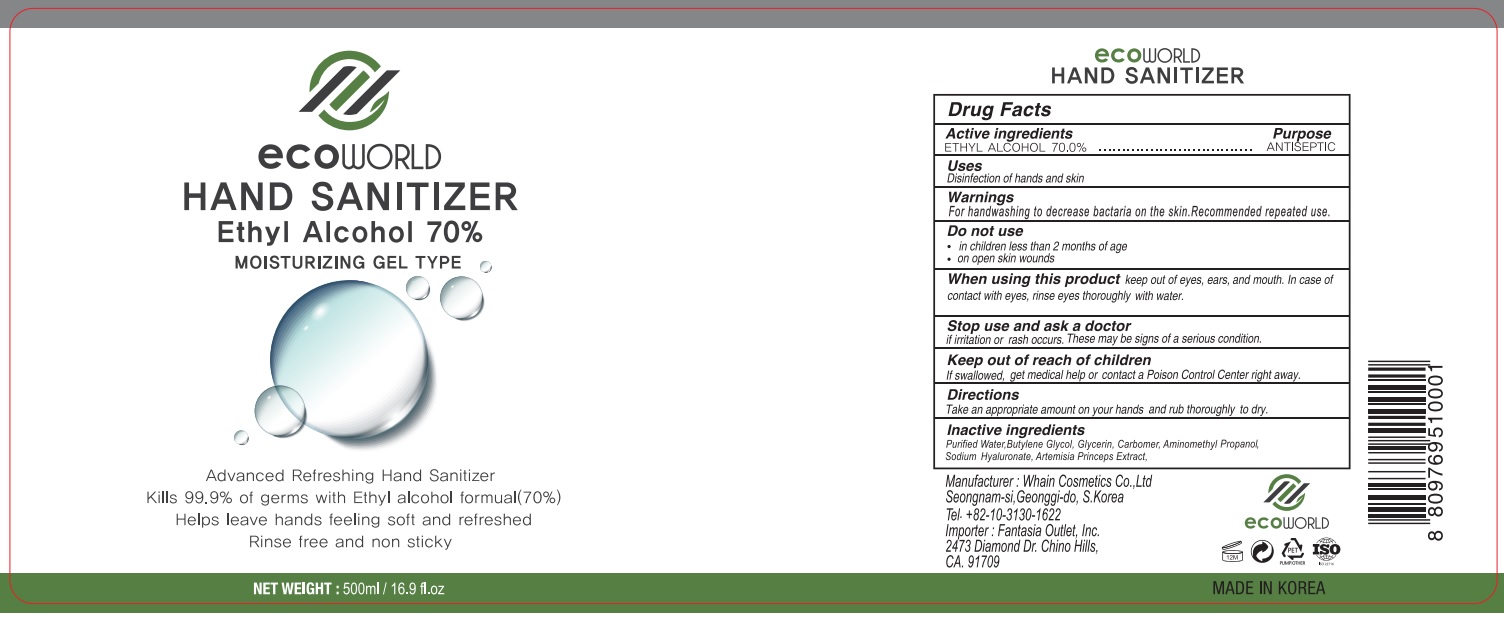 DRUG LABEL: Ecoworld Hand Sanitizer
NDC: 73823-500 | Form: GEL
Manufacturer: WHAIN COSMETIC
Category: otc | Type: HUMAN OTC DRUG LABEL
Date: 20200913

ACTIVE INGREDIENTS: ALCOHOL 350 mL/500 mL
INACTIVE INGREDIENTS: GLYCERIN; HYALURONATE SODIUM; BUTYLENE GLYCOL; WATER; ARTEMISIA PRINCEPS LEAF; AMINOMETHYLPROPANOL; CARBOMER HOMOPOLYMER, UNSPECIFIED TYPE

[WHAIN COSMETIC] Ecoworld Hand Sanitizer 500 ml : 73823-500